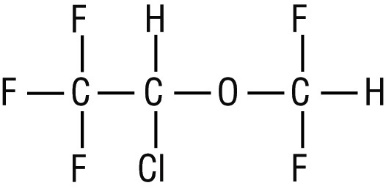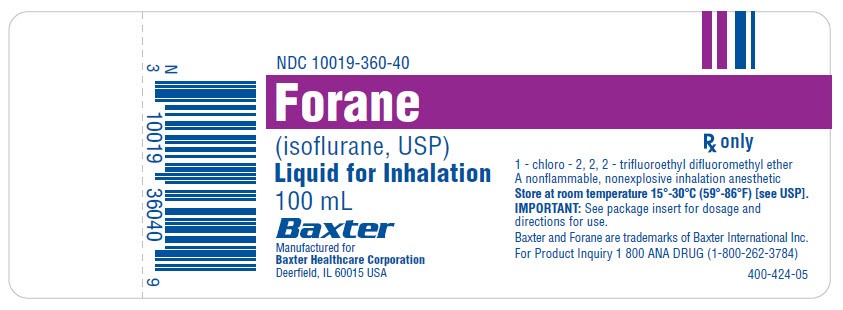 DRUG LABEL: FORANE
NDC: 10019-360 | Form: INHALANT
Manufacturer: Baxter Healthcare Corporation
Category: prescription | Type: HUMAN PRESCRIPTION DRUG LABEL
Date: 20241209

ACTIVE INGREDIENTS: ISOFLURANE 1 mL/1 mL

HIGHLIGHTS OF PRESCRIBING INFORMATION

These highlights do not include all the information needed to use FORANE safely and effectively. See full prescribing information for FORANE.
FORANE (isoflurane, USP) liquid for inhalation
Initial U.S. Approval: 1979

1 INDICATIONS AND USAGE

FORANE, a general anesthetic, is an inhalation agent indicated for induction and maintenance of general anesthesia. (1)

2 DOSAGE AND ADMINISTRATION

- FORANE should be administered only by persons trained in the administration of general anesthesia. FORANE should only be delivered using a vaporizer specifically designed and designated for use with isoflurane. (2)
- The administration of general anesthesia must be individualized and titrated based on the patient’s age and clinical status. (2)

3 DOSAGE FORMS AND STRENGTHS

Liquid (stable): 100% (3)

4 CONTRAINDICATIONS

- Patients in whom general anesthesia is contraindicated (4)
- Patients with known sensitivity to FORANE or other halogenated agents (4)
- Patients with known or suspected genetic susceptibility to malignant hyperthermia (4)
- Patients with a history of confirmed hepatitis due to a halogenated inhalational anesthetic or a history of unexplained moderate to severe hepatic dysfunction (e.g., jaundice associated with fever and/or eosinophilia) after anesthesia with FORANE or other halogenated inhalational anesthetics (4)

5 WARNINGS AND PRECAUTIONS

- Malignant Hyperthermia: Malignant hyperthermia may occur, especially in individuals with known or suspected susceptibility based on genetic factors or family history. Discontinue triggering agents, administer intravenous dantrolene sodium, and apply supportive therapies. (5.1)
- Perioperative Hyperkalemia: Perioperative hyperkalemia may occur. Patients with latent or overt neuromuscular disease, particularly with Duchenne muscular dystrophy, appear to be most vulnerable. Early, aggressive intervention is recommended. (5.2)
- Hepatic Reactions: May cause sensitivity hepatitis in patients sensitized by previous exposure to halogenated anesthetics. Approach repeated anesthesia with caution. (5.3)
- Hypersensitivity Reactions: Allergic-type hypersensitivity reactions, including anaphylaxis, have been reported with FORANE. (5.4)
- Abortions: Increased blood loss comparable to that seen with halothane has been observed in patients undergoing abortions. (5.5)
- QT Prolongation: Carefully monitor cardiac rhythm when administering FORANE to susceptible patients. (5.6)
- Interactions with Desiccated Carbon Dioxide (CO2) Absorbents: May react with desiccated CO2 absorbents to produce carbon monoxide. Replace desiccated CO2 absorbent before administration of FORANE. (5.7)
- Pediatric Neurotoxicity: In developing animals, exposures greater than 3 hours cause neurotoxicity. Weigh benefits against potential risks when considering elective procedures in children under 3 years old. (5.8)

6 ADVERSE REACTIONS

Most common adverse reactions (incidence ≥ 5%) are agitation, cough, breath holding, nausea, chills/shivering, vomiting, laryngospasm, delirium. (6.1)

To report SUSPECTED ADVERSE REACTIONS, contact Baxter Healthcare Corporation at 1-800-262-3784 or FDA at 1-800-FDA-1088 or www.fda.gov/medwatch.

7 DRUG INTERACTIONS

- Concomitant use of N2O and/or opioids reduces the MAC of FORANE. Adjust dose accordingly. (7.1, 7.2)
- FORANE decreases the doses of neuromuscular blocking agents required. Adjust dose accordingly. (7.3)

8 USE IN SPECIFIC POPULATIONS

- Geriatric Use: The minimum alveolar concentration (MAC) of FORANE decreases with increasing patient age. (8.5)

FULL PRESCRIBING INFORMATION

1 INDICATIONS AND USAGE

FORANE (isoflurane, USP) may be used for induction and maintenance of general anesthesia. Adequate data have not been developed to establish its application in obstetrical anesthesia.

2 DOSAGE AND ADMINISTRATION

2.1 Important Dosage and Administration Information

FORANE should be administered only by persons trained in the administration of general anesthesia. Facilities for maintenance of a patent airway, artificial ventilation, oxygen enrichment, and circulatory resuscitation must be immediately available.

FORANE is administered by inhalation. FORANE should be delivered from a vaporizer specifically designed for use with FORANE. Dosage for induction and maintenance must be individualized and titrated to the desired effect according to the patient’s age and clinical status. With the exception of neonates, the minimum alveolar concentration (MAC) of isoflurane decreases with increasing patient age.

Nitrous oxide decreases the MAC of FORANE (see Table 1). Opioids decrease the MAC of FORANE [see Drug Interactions (7)]. FORANE potentiates the muscle relaxant effect of all neuromuscular blockers and decreases the required doses of neuromuscular blocking agents [see Drug Interactions (7)]. The dose should be adjusted accordingly. All patients anesthetized with FORANE should be continually monitored (e.g., monitoring of the electrocardiogram, blood pressure, oxygen saturation, and end tidal CO2). FORANE is a profound respiratory depressant. Excessive respiratory depression may be related to depth of anesthesia and respond to decreasing the inspired concentration of FORANE. The depressant effect is accentuated by concurrent use of opioids and other respiratory depressants. Respiration should be closely monitored and assisted or controlled ventilation employed when necessary.

2.2 Premedication

Premedication should be selected according to the need of the individual patient, taking into account that secretions are weakly stimulated by FORANE, and the heart rate tends to be increased.

2.3 Induction

Induction with FORANE in oxygen or in combination with oxygen-nitrous oxide mixtures may produce coughing, breath holding, laryngospasm and bronchospasm, which increases with the concentration of isoflurane. These difficulties may be avoided by the use of a hypnotic dose of an ultra-short-acting barbiturate. Inspired concentrations of 1.5 to 3% isoflurane usually produce surgical anesthesia in 7 to 10 minutes.

2.4 Maintenance

FORANE MAC values according to age are shown below:

Table 1: Effect of Age on Minimum Alveolar Concentration of FORANE
Age | Average MAC Value In 100% Oxygen | Average MAC Value In 30% Oxygen and 70% N2 O
Preterm neonates less than 32 weeks gestational age | 1.28%
Preterm neonates 32-37 weeks gestational age | 1.41%
0-1 month | 1.60%
1-6 months | 1.87%
6-12 months | 1.80%
1-5 years | 1.60%
6-10 years | 1.45%
11-18 years | 1.38%
19-30 years | 1.28% | 0.56%
31-55 years | 1.15% | 0.50%
55-83 years | 1.05% | 0.37%

Dosage for induction and maintenance must be individualized and titrated to the desired effect according to the patient’s age and clinical status.

Surgical levels of anesthesia may be sustained with a 1 to 2.5% concentration when nitrous oxide is used concomitantly. An additional 0.5 to 1% may be required when isoflurane is given using oxygen alone. If added relaxation is required, supplemental doses of neuromuscular blocking agents may be used.

The level of blood pressure during maintenance is an inverse function of FORANE concentration in the absence of other complicating problems. Excessive decreases may be due to depth of anesthesia and in such instances may be corrected by lightening anesthesia.

FORANE causes a dose-dependent reduction in systemic vascular resistance and blood pressure. Particular care must be taken when selecting the dosage for patients who are hypovolemic, hypotensive, or otherwise hemodynamically compromised, e.g., due to concomitant medications.

FORANE markedly increases cerebral blood flow at deeper levels of anesthesia to produce a transient increase in intracranial pressure. In patients with or at risk for elevations of intracranial pressure (ICP), administer isoflurane in conjunction with ICP-reducing strategies, as clinically appropriate.

2.5 Use in Patients with Coronary Artery Disease

Regardless of the anesthetics employed, maintenance of normal hemodynamics is important to the avoidance of myocardial ischemia in patients with coronary artery disease.

FORANE can cause dose-dependent coronary vasodilation and has been shown to divert blood from collateral-dependent myocardium to normally perfused areas in an animal model (“coronary steal”). The extent to which coronary steal occurs in patients with steal-prone coronary anatomy is unclear. Monitor for signs of inadequate myocardial perfusion via hemodynamic monitors (e.g., ECG, blood pressure) during isoflurane administration. Consider additional cardiac monitoring in patients with known coronary artery disease, as clinically necessary.

3 DOSAGE FORMS AND STRENGTHS

Isoflurane is a clear, colorless, stable liquid containing no additives or chemical stabilizers, 100% isoflurane.

4 CONTRAINDICATIONS

FORANE is contraindicated in patients:

- in whom general anesthesia is contraindicated.
- with known sensitivity to FORANE or to other halogenated agents [see Warnings and Precautions (5.3)].
- with known or suspected genetic susceptibility to malignant hyperthermia [see Warnings and Precautions (5.1), Clinical Pharmacology (12.5)].
- with a history of confirmed hepatitis due to a halogenated inhalational anesthetic or a history of unexplained moderate to severe hepatic dysfunction (e.g., jaundice associated with fever and/or eosinophilia) after anesthesia with isoflurane or other halogenated inhalational anesthetics.

5 WARNINGS AND PRECAUTIONS

5.1 Malignant Hyperthermia

In susceptible individuals, volatile anesthetic agents, including FORANE, may trigger malignant hyperthermia, a skeletal muscle hypermetabolic state leading to high oxygen demand. Fatal outcomes of malignant hyperthermia have been reported.

The risk of developing malignant hyperthermia increases with the concomitant administration of succinylcholine and volatile anesthetic agents. FORANE can induce malignant hyperthermia in patients with known or suspected susceptibility based on genetic factors or family history, including those with certain inherited ryanodine receptor (RYR1) or dihydropyridine receptor (CACNA1S) variants [see Contraindications (4), Clinical Pharmacology (12.5)].

Signs consistent with malignant hyperthermia may include hyperthermia, hypoxia, hypercapnia, muscle rigidity (e.g., jaw muscle spasm), tachycardia (e.g., particularly that unresponsive to deepening anesthesia or analgesic medication administration), tachypnea, cyanosis, arrhythmias, hypovolemia, and hemodynamic instability. Skin mottling, coagulopathies, and renal failure may occur later in the course of the hypermetabolic process.

Successful treatment of malignant hyperthermia depends on early recognition of the clinical signs. If malignant hyperthermia is suspected, discontinue all triggering agents (i.e., volatile anesthetic agents and succinylcholine), administer intravenous dantrolene sodium, and initiate supportive therapies. Consult prescribing information for intravenous dantrolene sodium for additional information on patient management. Supportive therapies include administration of supplemental oxygen and respiratory support based on clinical need, maintenance of hemodynamic stability and adequate urinary output, management of fluid and electrolyte balance, correction of acid base derangements, and institution of measures to control rising temperature.

5.2 Perioperative Hyperkalemia

Use of inhaled anesthetic agents has been associated with rare increases in serum potassium levels that have resulted in cardiac arrhythmias and death in pediatric patients during the postoperative period. Patients with latent as well as overt neuromuscular disease, particularly Duchenne muscular dystrophy, appear to be most vulnerable. Concomitant use of succinylcholine has been associated with most, but not all, of these cases. These patients also experienced significant elevations in serum creatinine kinase levels and, in some cases, changes in urine consistent with myoglobinuria. Despite the similarity in presentation to malignant hyperthermia, none of these patients exhibited signs or symptoms of muscle rigidity or hypermetabolic state. Early and aggressive intervention to treat the hyperkalemia and resistant arrhythmias is recommended, as is subsequent evaluation for latent neuromuscular disease.

5.3 Hepatic Reactions

Cases of mild, moderate and severe postoperative hepatic dysfunction or hepatitis with or without jaundice, including fatal hepatic necrosis and hepatic failure, have been reported with FORANE.

Such reactions can represent hypersensitivity hepatitis, a known risk of exposure to halogenated anesthetics, including FORANE. As with other halogenated anesthetic agents, FORANE may cause sensitivity hepatitis in patients who have been sensitized by previous exposure to halogenated anesthetics [see Contraindications (4)].

Clinical judgment should be exercised when FORANE is used in patients with underlying hepatic conditions or under treatment with drugs known to cause hepatic dysfunction [see Contraindications (4)].

As with all halogenated anesthetics, repeated anesthetics within a short period of time may result in increased effects, particularly in patients with underlying hepatic conditions, or additive effects in patients treated with drugs known to cause hepatic dysfunction. Evaluate the need for repeated exposure in each individual patient and adjust the dose of FORANE based on signs and symptoms of adequate depth of anesthesia if repeated exposure in a short period of time is clinically indicated.

5.4 Hypersensitivity Reactions

Allergic-type hypersensitivity reactions, including anaphylaxis, have been reported with FORANE. Manifestations of such reactions have included hypotension, rash, difficulty breathing and cardiovascular collapse

5.5 Abortions

Increased blood loss comparable to that seen with halothane has been observed in patients undergoing abortions.

5.6 QT Prolongation

QT prolongation, with rare instances of torsade de pointes, have been reported. Monitor QT interval when administering FORANE to susceptible patients (e.g., patients with congenital Long QT Syndrome or patients taking drugs that can prolong the QT interval).

5.7 Interactions with Desiccated Carbon Dioxide Absorbents

FORANE, like some other inhalational anesthetics, can react with desiccated carbon dioxide (CO^2) absorbents to produce carbon monoxide, which may result in elevated levels of carboxyhemoglobin in some patients. Barium hydroxide lime and soda lime become desiccated when fresh gases are passed through the CO^2 absorber canister at high flow rates over many hours or days. When a clinician suspects that CO^2 absorbent may be desiccated, it should be replaced before the administration of FORANE.

The color indicator of most CO2 absorbents does not necessarily change as a result of desiccation. Therefore, the lack of significant color change should not be taken as assurance of adequate hydration of the CO2 absorbent material. CO2 absorbents should be replaced routinely regardless of the state of color indicator following current manufacturer’s guidelines for use of anesthesiology equipment.

5.8 Pediatric Neurotoxicity

Published animal studies demonstrate that the administration of anesthetic and sedation drugs that block NMDA receptors and/or potentiate GABA activity increase neuronal apoptosis in the developing brain and result in long-term cognitive deficits when used for longer than 3 hours. The clinical significance of these findings is not clear. However, based on the available data, the window of vulnerability to these changes is believed to correlate with exposures in the third trimester of gestation through the first several months of life, but may extend out to approximately three years of age in humans [see Use in Specific Populations (8.1, 8.4), Nonclinical Toxicology (13.2)].

Some published studies in children suggest that similar deficits may occur after repeated or prolonged exposures to anesthetic agents early in life and may result in adverse cognitive or behavioral effects. These studies have substantial limitations, and it is not clear if the observed effects are due to the anesthetic/sedation drug administration or other factors such as the surgery or underlying illness.

Anesthetic and sedation drugs are a necessary part of the care of children needing surgery, other procedures, or tests that cannot be delayed, and no specific medications have been shown to be safer than any other. Decisions regarding the timing of any elective procedures requiring anesthesia should take into consideration the benefits of the procedure weighed against the potential risks.

5.9 Laboratory Tests

Transient increases in BSP retention, blood glucose and serum creatinine with decrease in BUN, serum cholesterol and alkaline phosphatase have been observed.

6 ADVERSE REACTIONS

6.1 Clinical Trials Experience

The following adverse reactions were identified from controlled clinical trials of adult and pediatric subjects exposed to FORANE. The trials were conducted using a variety of pre-medications, other anesthetics, and surgical procedures of varying lengths.

The most serious reported adverse reactions in alphabetical order are agitation, arrhythmia, breath holding, elevated liver enzyme, hypotension and laryngospasm.

The most frequent adverse reactions (incidence ≥ 5%) described in Table 1 are agitation, breath holding, chills/shivering, cough, delirium, laryngospasm, nausea, and vomiting.

Adverse reactions with an incidence between 1% and 5% are provided in Table 2.

Adverse reactions with an incidence less than 1% are provided in Table 3.

Because clinical trials are conducted under widely varying conditions, adverse reaction rates observed in the clinical trials of a drug cannot be directly compared to rates in the clinical trials of another drug and may not reflect the rates observed in practice.

Table 2: Adverse Reactions ≥ 5%
System Organ Class (SOC) | Adverse Reaction |  | Frequency
PSYCHIATRIC DISORDERS | Delirium |  | 6.2% (N=2830)
NERVOUS SYSTEM DISORDERS | Agitation (Excitement) | Induction | 51.8% (N=515) [Represents patients not receiving intravenous agents or neuromuscular blocking agents for intubation (i.e., patients receiving inhalation induction).]
RESPIRATORY, THORACIC, AND MEDIASTINAL DISORDERS | Breath holding | Induction | 23.9% (N=515)
RESPIRATORY, THORACIC, AND MEDIASTINAL DISORDERS | Cough | Induction | 28.2% (N=515)
RESPIRATORY, THORACIC, AND MEDIASTINAL DISORDERS | Laryngospasm | Induction | 8.0% (N=515)
GASTROINTESTINAL DISORDERS | Nausea | Recovery | 15.4 % (N=2830)
GASTROINTESTINAL DISORDERS | Vomiting | Recovery | 9.5% (N=2830)
GENERAL DISORDERS AND ADMINISTRATIVE SITE CONDITIONS | Chills/shivering |  | 14.0% (N=1691) [Reflects the number of patients with recorded body temperature measurements.]

Table 3: Adverse Reactions between 1% and 5%
System Organ Class (SOC) | Adverse Reaction |  | Frequency
NERVOUS SYSTEM DISORDERS | Movement | Maintenance | 1.8% (N=2830)
CARDIAC DISORDERS | Ventricular arrhythmia (Intraoperative) | Induction | 2.1% (N=2161)
CARDIAC DISORDERS | Ventricular arrhythmia (Intraoperative) | Maintenance | 2.7% (N=2253)
CARDIAC DISORDERS | Nodal arrhythmia (Intraoperative) | Induction | 4.0% (N=2161)
CARDIAC DISORDERS | Nodal arrhythmia (Intraoperative) | Maintenance | 1.7% (N=2253)
CARDIAC DISORDERS | Atrial arrhythmia (Intraoperative) | Induction | 1.6% (N=2161)
CARDIAC DISORDERS | Atrial arrhythmia (Intraoperative) | Maintenance | 2.2% (N=2253)
CARDIAC DISORDERS | Arrhythmia (Postoperative) |  | 1.1% (N=2830)
RESPIRATORY, THORACIC, AND MEDIASTINAL DISORDERS | Breath holding | Maintenance | 1.1% (N=359) [Represents patients not receiving intravenous agents or neuromuscular blocking agents for intubation (i.e., patients receiving inhalation induction).]
RESPIRATORY, THORACIC, AND MEDIASTINAL DISORDERS | Cough | Maintenance | 4.2 % (N=359)

Table 4: Adverse Reactions less than 1%
System Organ Class (SOC) | Adverse Reaction |  | Frequency
PSYCHIATRIC DISORDERS | Mood changes |  | 0.3% (N=2830)
PSYCHIATRIC DISORDERS | Nightmare |  | 0.4% (N=2175) [Reflects the number of patients interviewed by a physician in the recovery period.]
NERVOUS SYSTEM DISORDERS | Convulsive pattern on electroencephalogram |  | 0.5% (N=200) [Reflects the number of recorded electroencephalograms.]
NERVOUS SYSTEM DISORDERS | Seizure |  | 0.04% (N=2830)
VASCULAR DISORDERS | Hypotension | Postoperative | 0.3% (N=2830)
VASCULAR DISORDERS | Hypertension | Postoperative | 0.1% (N=2830)
RESPIRATORY, THORACIC, AND MEDIASTINAL DISORDERS | Laryngospasm | Maintenance | 0.8% (N=359) [Represents patients not receiving intravenous agents or neuromuscular blocking agents for intubation (i.e., patients receiving inhalation induction).]
RESPIRATORY, THORACIC, AND MEDIASTINAL DISORDERS | Secretions | Induction | 0.2% (N=515)
RESPIRATORY, THORACIC, AND MEDIASTINAL DISORDERS | Secretions | Maintenance | 0.0% (N=359)
GASTROINTESTINAL DISORDERS | Vomiting | Induction | 0.8% (N=515)
GASTROINTESTINAL DISORDERS | Retching | Induction | 1.0% (N=515)
GASTROINTESTINAL DISORDERS | Retching | Maintenance | 0.8% (N=359)
SKIN AND SUBCUTANEOUS TISSUE DISORDERS | Diaphoresis | Induction | 0.2% (N=515)
SKIN AND SUBCUTANEOUS TISSUE DISORDERS | Diaphoresis | Maintenance | 0.0% (N=359)

The following adverse reactions (see Table 5) were observed, but due to limited data, frequency could not be determined.

Table 5: Adverse Reactions with Unknown Frequency
System Organ Class (SOC) | Adverse Reaction
Metabolism and Nutrition Disorders: | Blood glucose increased
Psychiatric Disorders: | Confused state, Nervousness
Nervous System Disorders: | Ataxia; Dizziness; Drowsiness; Intellectual function decrease
Vascular Disorders: | Hypotension (Intraoperative); Hypertension (Intraoperative)
Hepatobiliary Disorders: | Blood bilirubin increased; Bromsulphthalein clearance decreased; Alanine aminotransferase increased; Aspartate aminotransferase increased; Blood alkaline phosphatase increased; Blood lactate dehydrogenase increased
Musculoskeletal, Connective Tissue and Bone Disorders: | Myalgia
General Disorders and Administrative Site Conditions: | Asthenia; Fatigue

6.2 Post-Marketing Experience

The following adverse reactions have been identified during post-approval use of FORANE. Because these reactions are reported voluntarily from a population of uncertain size, it is not always possible to reliably estimate their frequency or establish a causal relationship to drug exposure.

Post-marketing adverse reactions are listed by MedDRA System Organ Class (SOC), then by preferred term in order of decreasing severity.

BLOOD AND LYMPHATIC SYSTEM DISORDERS: Carboxyhemoglobin increased

IMMUNE SYSTEM DISORDERS: Anaphylactic reaction

METABOLISM AND NUTRITION DISORDERS: Hyperkalemia in patients with underlying myopathies

PSYCHIATRIC DISORDERS: Withdrawal syndrome (following multi-day exposure; symptoms include seizure, hallucination, ataxia, agitation, confusion)

NERVOUS SYSTEM DISORDERS: Brain edema, Intracranial pressure increased, Migraine, Myoclonus, Nystagmus, Pupils unequal, Headache

CARDIAC DISORDERS: Cardiac arrest, Ventricular fibrillation, Torsade de pointes, Myocardial infarction, Myocardial ischemia, Atrioventricular block complete, Atrioventricular block second degree, Atrial fibrillation, Electrocardiogram QT prolonged, Atrioventricular block first degree, Ventricular tachycardia, Ventricular extrasystoles, Tachycardia, Bradycardia, Cardiac output decreased

VASCULAR DISORDERS: Flushing

RESPIRATORY, THORACIC, AND MEDIASTINAL DISORDERS: Apnea, Hypoxia, Bronchospasm, Airway obstruction, Respiratory depression, Hypercapnia, Stridor, Hiccough

GASTROINTESTINAL DISORDERS: Pancreatitis

HEPATOBILIARY DISORDERS: Hepatic necrosis, Hepatic failure, Hepatitis fulminant, Cholestatic hepatitis, Hepatitis, Hepatic steatosis, Jaundice, Gamma-glutamyltransferase increased

SKIN AND SUBCUTANEOUS TISSUE DISORDERS: Rash

MUSCULOSKELETAL, CONNECTIVE TISSUE AND BONE DISORDERS:Rhabdomyolysis

RENAL AND URINARY DISORDERS: Acute renal failure**, Oliguria**

GENERAL DISORDERS AND ADMINISTRATION SITE CONDITIONS: Malignant hyperthermia, hypothermia

INJURY, POISONING, AND PROCEDURAL COMPLICATIONS*: Unwanted awareness during anesthesia; Dyspnea, Bronchospasm, Stridor, Cough, Dizziness, Paresthesia, Hepatic reactions, Flushing, Rash, Contact dermatitis, Erythema, Periorbital edema, Eye irritation, Conjunctival hyperemia, Headache

*All reactions categorized within this SOC, with the exception of, Unwanted awareness during anesthesia, were from occupational exposure in non-patients.

**Cases of acute renal failure and oliguria have been reported after isoflurane anesthesia. These events may be secondary to hypotension or other effects of isoflurane.

7 DRUG INTERACTIONS

7.1 Opioids

Opioids decrease the Minimum Alveolar Concentration (MAC) of FORANE. Opioids such as fentanyl and its analogues, when combined with FORANE, may lead to a synergistic fall in blood pressure and respiratory rate.

7.2 Nitrous Oxide

Nitrous oxide decreases the MAC of FORANE [see Dosage and Administration (2.1)].

7.3 Neuromuscular Blocking Agents

FORANE potentiates the muscle relaxant effect of all neuromuscular blocking agents and decreases the required doses of neuromuscular blocking agents. In general, anesthetic concentrations of FORANE at equilibrium reduce the ED95 of succinylcholine, atracurium, pancuronium, rocuronium and vecuronium by approximately 25 to 40% or more compared to N2O/opioid anesthesia. If added relaxation is required, supplemental doses of neuromuscular blocking agents may be used.

7.4 Adrenaline

FORANE is similar to sevoflurane in the sensitization of the myocardium to arrhythmogenic effect of exogenously administered adrenaline. Doses of adrenaline greater than 5mcg/kg, when administered submucosally may produce multiple ventricular arrhythmias.

7.5 Calcium Antagonists

FORANE may lead to marked hypotension in patients treated with calcium antagonists.

7.6 Concomitant Use with Beta Blockers

Concomitant use of beta blockers may exaggerate the cardiovascular effects of inhalational anesthetics, including hypotension and negative inotropic effects.

7.7 Concomitant Use with MAO Inhibitors

Concomitant use of MAO inhibitors and inhalational anesthetics may increase the risk of hemodynamic instability during surgery or medical procedures.

8 USE IN SPECIFIC POPULATIONS

8.1 Pregnancy

Risk Summary

There are no adequate and well-controlled studies in pregnant women. In animal reproduction studies, embryofetal toxicity was noted in pregnant mice exposed to 0.075% (increased post implantation losses) and 0.3% isoflurane (increased post implantation losses and decreased livebirth index) during organogenesis.

Published studies in pregnant primates demonstrate that the administration of anesthetic and sedation drugs that block NMDA receptors and/or potentiate GABA activity during the period of peak brain development increases neuronal apoptosis in the developing brain of the offspring when used for longer than 3 hours. There are no data on pregnancy exposures in primates corresponding to periods prior to the third trimester in humans (see Data).

The estimated background risk of major birth defects and miscarriage for the indicated population is unknown. All pregnancies have a background risk of birth defect, loss, or other adverse outcomes. In the U.S. general population, the estimated background risk of major birth defects and miscarriage in clinically recognized pregnancies is 2-4% and 15-20%, respectively.

Data

Animal Data

Pregnant rats were exposed to isoflurane at concentrations of 0%, 0.1%, or 0.4% for two hours per day during organogenesis (Gestational Days 6-15). Isoflurane did not cause malformations or clear maternal toxicity under these conditions.

Pregnant mice exposed to isoflurane at concentrations of 0%, 0.075%, or 0.30% for 2 hours per day during organogenesis (Gestational Days 6-15). Isoflurane increased fetal toxicity (higher post implantation losses at 0.075 and 0.3% groups and significantly lower live-birth index in the 0.3% isoflurane treatment group). Isoflurane did not cause malformations or clear maternal toxicity under these conditions.

Pregnant rats were exposed to concentrations of isoflurane at 0%, 0.1%, or 0.4% for 2 hours per day during late gestation (GD 15-20). Animals appeared slightly sedated during exposure. No adverse effects on the offspring or evidence of maternal toxicity were reported. This study did not evaluate neurobehavioral function including learning and memory in the first generation (F1) of pups.

In a published study in primates, administration of an anesthetic dose of ketamine for 24 hours on Gestation Day 122 increased neuronal apoptosis in the developing brain of the fetus. In other published studies, administration of either isoflurane or propofol for 5 hours on Gestation Day 120 resulted in increased neuronal and oligodendrocyte apoptosis in the developing brain of the offspring. With respect to brain development, this time period corresponds to the third trimester of gestation in the human. The clinical significance of these findings is not clear; however, studies in juvenile animals suggest neuroapoptosis correlates with long-term cognitive deficits [see Warnings and Precautions (5.8), Nonclinical Toxicology (13.2)].

8.2 Lactation

Due to insufficient information regarding the excretion of isoflurane in human milk, the potential risks and benefits for each specific patient should be carefully considered before isoflurane is administered to nursing women.

8.4 Pediatric Use

During the induction of anesthesia, saliva flow and tracheobronchial secretion can increase and can be the cause of larynogospasm, particularly in children.

Published juvenile animal studies demonstrate that the administration of anesthetic and sedation drugs, such as FORANE, that either block NMDA receptors or potentiate the activity of GABA during the period of rapid brain growth or synaptogenesis, results in widespread neuronal and oligodendrocyte cell loss in the developing brain and alterations in synaptic morphology and neurogenesis. Based on comparisons across species, the window of vulnerability to these changes is believed to correlate with exposures in the third trimester of gestation through the first several months of life, but may extend out to approximately 3 years of age in humans.

In primates, exposure to 3 hours of ketamine that produced a light surgical plane of anesthesia did not increase neuronal cell loss, however, treatment regimens of 5 hours or longer of isoflurane increased neuronal cell loss. Data from isoflurane-treated rodents and ketamine-treated primates suggest that the neuronal and oligodendrocyte cell losses are associated with prolonged cognitive deficits in learning and memory. The clinical significance of these nonclinical findings is not known, and healthcare providers should balance the benefits of appropriate anesthesia in pregnant women, neonates, and young children who require procedures with the potential risks suggested by the nonclinical data [see Warnings and Precautions (5.8), Nonclinical Toxicology (13.2)].

8.5 Geriatric Use

The minimum alveolar concentration (MAC) of isoflurane decreases with increasing patient age. The dose should be adjusted accordingly [see Dosage and Administration (2.4)].

10 OVERDOSAGE

The symptoms of overdosage of FORANE can present as a deepening of anesthesia, cardiac and/or respiratory depression in spontaneously breathing patients, and cardiac depression in ventilated patients in whom hypercapnia and hypoxia may occur only at a late stage.

In the event of overdosage, or what may appear to be overdosage, the following action should be taken, as appropriate:

Stop drug administration, establish a clear airway, and initiate assisted or controlled ventilation with pure oxygen. Monitor cardiovascular function and manage signs of poor end-organ perfusion as clinically indicated.

11 DESCRIPTION

FORANE (isoflurane, USP), a nonflammable liquid administered by vaporizing, is a general inhalation anesthetic drug. It is 1-chloro-2,2,2-trifluoroethyl difluoromethyl ether, and its structural formula is:

Some physical constants are:

Molecular weight |  |  | 184.5
Boiling point at 760 mm Hg |  |  | 48.5°C
Refractive index n 20⸑D |  |  | 1.2990-1.3005
Specific gravity 25°/25°C |  |  | 1.496
Vapor pressure in mm Hg** | 20°C |  | 238
 | 25°C |  | 295
 | 30°C |  | 367
 | 35°C |  | 450
**Equation for vapor pressure calculation:
log10Pvap = A + B⸑T where: |  | A = 8.056
 |  | B = -1664.58
 |  | T = °C + 273.16 (Kelvin)

Partition coefficients at 37°C

Water/gas | 0.61
Blood/gas | 1.43
Oil/gas | 90.8

Partition coefficients at 25°C – rubber and plastic

Conductive rubber/gas | 62.0
Butyl rubber/gas | 75.0
Polyvinyl chloride/gas | 110.0
Polyethylene/gas | ~2.0
Polyurethane/gas | ~1.4
Polyolefin/gas | ~1.1
Butyl acetate/gas | ~2.5
Purity by gas chromatography | >99.9%
Lower limit of flammability in oxygen or nitrous oxide at 9 joules/sec. and 23°C | None
Lower limit of flammability in oxygen or nitrous oxide at 900 joules/sec. and 23°C | Greater than useful concentration in anesthesia.

Isoflurane is a clear, colorless, stable liquid containing no additives or chemical stabilizers. Isoflurane has a mildly pungent, musty, ethereal odor. Samples stored in indirect sunlight in clear, colorless glass for five years, as well as samples directly exposed for 30 hours to a 2 amp, 115 volt, 60 cycle long wave U.V. light were unchanged in composition as determined by gas chromatography. Isoflurane in one normal sodium methoxide-methanol solution, a strong base, for over six months consumed essentially no alkali, indicative of strong base stability. Isoflurane does not decompose in the presence of soda lime (at normal operating temperatures), and does not attack aluminum, tin, brass, iron or copper.

12 CLINICAL PHARMACOLOGY

12.2 Pharmacodynamics

Induction of and recovery from isoflurane anesthesia are rapid. Isoflurane has a mild pungency which limits the rate of induction, although excessive salivation or tracheobronchial secretions do not appear to be stimulated. Pharyngeal and laryngeal reflexes are readily obtunded. The level of anesthesia may be changed rapidly with isoflurane. Isoflurane is a profound respiratory depressant. As anesthetic dose is increased, tidal volume decreases and respiratory rate is unchanged. This depression is partially reversed by surgical stimulation, even at deeper levels of anesthesia. Isoflurane evokes a sigh response reminiscent of that seen with diethyl ether and enflurane, although the frequency is less than with enflurane.

Blood pressure decreases with induction of anesthesia but returns toward normal with surgical stimulation. Progressive increases in depth of anesthesia produce corresponding decreases in blood pressure. Nitrous oxide diminishes the inspiratory concentration of isoflurane required to reach a desired level of anesthesia and may reduce the arterial hypotension seen with isoflurane alone. Heart rhythm is remarkably stable. With controlled ventilation and normal PaCO2, cardiac output is maintained despite increasing depth of anesthesia, primarily through an increase in heart rate which compensates for a reduction in stroke volume. The hypercapnia which attends spontaneous ventilation during isoflurane anesthesia further increases heart rate and raises cardiac output above awake levels.

Muscle relaxation is often adequate for intra-abdominal operations at normal levels of anesthesia. Complete muscle paralysis can be attained with small doses of neuromuscular blocking agents. ALL COMMONLY USED NEUROMUSCULAR BLOCKING AGENTS ARE MARKEDLY POTENTIATED WITH ISOFLURANE, THE EFFECT BEING MOST PROFOUND WITH THE NONDEPOLARIZING TYPE. Neostigmine reverses the effect of nondepolarizing neuromuscular blocking agents in the presence of isoflurane. All commonly used neuromuscular blocking agents are compatible with isoflurane.

Isoflurane can produce coronary vasodilation at the arteriolar level in selected animal models; the drug is probably also a coronary dilator in humans. Isoflurane, like some other coronary arteriolar dilators, has been shown to divert blood from collateral dependent myocardium to normally perfused areas in an animal model (“coronary steal”). Clinical trials to date evaluating myocardial ischemia, infarction and death as outcome parameters have not established that the coronary arteriolar dilation property of isoflurane is associated with coronary steal or myocardial ischemia in patients with coronary artery disease.

12.3 Pharmacokinetics

Isoflurane undergoes minimal biotransformation in man. In the postanesthesia period, only 0.17% of the isoflurane taken up can be recovered as urinary metabolites.

12.5 Pharmacogenomics

RYR1 and CACNA1S are polymorphic genes, and multiple pathogenic variants have been associated with malignant hyperthermia susceptibility (MHS) in patients receiving volatile anesthetic agents, including FORANE. Case reports as well as ex-vivo studies have identified multiple variants in RYR1 and CACNA1S associated with MHS. Variant pathogenicity should be assessed based on prior clinical experience, functional studies, prevalence information, or other evidence [see Contraindications (4), Warnings and Precautions (5.1)].

13 NONCLINICAL TOXICOLOGY

13.1 Carcinogenesis, Mutagenesis, Impairment of Fertility

Carcinogenesis

Swiss ICR mice were given isoflurane to determine whether such exposure might induce neoplasia. Isoflurane was given at 1/2, 1/8 and 1/32 MAC for four in-utero exposures and for 24 exposures to the pups during the first nine weeks of life. The mice were killed at 15 months of age. The incidence of tumors in these mice was the same as in untreated control mice, which were given the same background gases, but not the anesthetic.

Mutagenesis

Isoflurane was negative in the in vivo mouse micronucleus and in vitro human lymphocyte chromosomal aberration assay. In published studies, isoflurane was negative in the in vitro bacterial reverse mutation assay (Ames test) in all strains tested (Salmonella typhimurium strains TA98, TA100, and TA1535) in the presence or absence of metabolic activation.

Impairment of Fertility

Male and female Sprague-Dawley rats were exposed to isoflurane at concentrations of 0%, 0.15%, and 0.60% (0, 1/8, and 1/2 MAC) 2 hours per day for 14 consecutive days prior to mating. Isoflurane had no effects on either male or female fertility.

13.2 Animal Toxicology and/or Pharmacology

Published studies in animals demonstrate that the use of anesthetic agents during the period of rapid brain growth or synaptogenesis results in widespread neuronal and oligodendrocyte cell loss in the developing brain and alterations in synaptic morphology and neurogenesis. Based on comparisons across species, the window of vulnerability to these changes is believed to correlate with exposures in the third trimester through the first several months of life but may extend out to approximately 3 years of age in humans.

In primates, exposure to 3 hours of an anesthetic regimen that produced a light surgical plane of anesthesia did not increase neuronal cell loss, however, treatment regimens of 5 hours or longer increased neuronal cell loss. Data in rodents and in primates suggest that the neuronal and oligodendrocyte cell losses are associated with subtle but prolonged cognitive deficits in learning and memory. The clinical significance of these nonclinical findings is not known, and healthcare providers should balance the benefits of appropriate anesthesia in neonates and young children who require procedures against the potential risks suggested by the nonclinical data [see Warnings and Precautions (5.3), Use in Specific Populations (8.1, 8.4)].

16 HOW SUPPLIED/STORAGE AND HANDLING

FORANE is available in the following presentations:

FILL | CONTAINER | PACK SIZE | NDC
100 mL | Amber-colored Glass | 6 Bottles | 10019-360-40
250 mL | Amber-colored Glass | 6 Bottles | 10019-360-60
250 mL | Aluminum | 6 Bottles | 10019-360-64

16.1 Safety and Handling

Occupational Caution

The following reactions have been reported following occupational exposure to isoflurane: dyspnea, bronchospasm, stridor, cough, dizziness, paresthesia, hepatic reactions, flushing rash, contact dermatitis, erythema, periorbital edema, eye irritation, conjunctival hyperemia, and headache.

There is no specific work exposure limit established for FORANE. However, the National Institute for Occupational Safety and Health Administration (NIOSH) recommends that no worker should be exposed at ceiling concentrations greater than 2 ppm of any halogenated anesthetic agent over a sampling period not to exceed one hour.

The predicted effects of acute overexposure by inhalation of FORANE include headache, dizziness or (in extreme cases) unconsciousness [see Overdosage (10)]. There are no documented adverse effects of chronic exposure to halogenated anesthetic vapors (Waste Anesthetic Gases or WAGs) in the workplace. Although results of some epidemiological studies suggest a link between exposure to halogenated anesthetics and increased health problems (particularly spontaneous abortion), the relationship is not conclusive. Since exposure to WAGs is one possible factor in the findings for these studies, operating room personnel, and pregnant women in particular, should minimize exposure. Precautions include adequate general ventilation in the operating room, the use of a well-designed and well-maintained scavenging system, work practices to minimize leaks and spills while the anesthetic agent is in use, and routine equipment maintenance to minimize leaks.

16.2 Storage

Store at room temperature 15°C - 30°C (59°F - 86°F). Isoflurane contains no additives and has been demonstrated to be stable at room temperature for periods in excess of five years.

17 PATIENT COUNSELING INFORMATION

Anesthesia providers need to obtain the following information from patients prior to administration of anesthesia:

- Medications they are taking, including herbal supplements
- Drug allergies, including allergic reactions to anesthetic agents (including hepatic sensitivity)
- Any history of severe reactions to prior administration of anesthetic
- If the patient or member of the patient’s family has a history of malignant hyperthermia or if the patient has a history of Duchenne muscular dystrophy or other latent neuromuscular disease

Anesthesia providers should inform patients of the following risks associated with FORANE:

Post-operative nausea and vomiting and respiratory adverse effects including coughing.

There is no information of the effects of FORANE following anesthesia on the ability to operate an automobile or other heavy machinery. However, patients should be advised that the ability to perform such tasks may be impaired after receiving anesthetic agents. Patients should not undertake hazardous tasks, such as driving, for at least 24 hours following administration of a general anesthetic.

Anesthesia providers should inform parents and caregivers of pediatric patients that emergence from anesthesia in children may evoke a brief state of agitation that may hinder cooperation.

Anesthesia providers should inform patients that FORANE, as well as other general anesthetics, may cause a slight decrease in intellectual function for 2 or 3 days following anesthesia. As with other anesthetics, small changes in moods and symptoms may persist for up to 6 days after administration.

Effect of anesthetic and sedation drugs on early brain development

Studies conducted in young animals and children suggest repeated or prolonged use of general anesthetic or sedation drugs in children younger than 3 years may have negative effects on their developing brains. Discuss with parents and caregivers the benefits, risks, and timing and duration of surgery or procedures requiring anesthetic and sedation drugs [see Warnings and Precautions (5.8)].

Baxter Logo

Manufactured for

Baxter Healthcare Corporation

Deerfield, IL 60015 USA

Baxter and Forane are trademarks of Baxter International Inc. or its subsidiaries,

For Product Inquiry 1 800 ANA DRUG (1-800-262-3784)

07-19-00-5984

PACKAGE/LABEL PRINCIPAL DISPLAY PANEL

Container Label

NDC 10019-360-40
Forane
(isoflurane, USP)
Liquid for Inhalation
100 mL
Baxter Logo
Manufactured for
Baxter Healthcare Corporation
Deerfield, IL 60015 USA

Rx only

1 – chloro – 2, 2, 2 – trifluoroethyl difluoromethyl ether
A nonflammable, nonexplosive inhalation anesthetic

Store at room temperature 15°-30°C (59°-86°) [see USP].

IMPORTANT: See package insert for dosage and
directions use.

Baxter and Forane are trademarks of Baxter International Inc.

For Product Inquiry 1 800 ANA DRUG (1-800-262-3784)

400-424-05

3 N 10019 36040 9